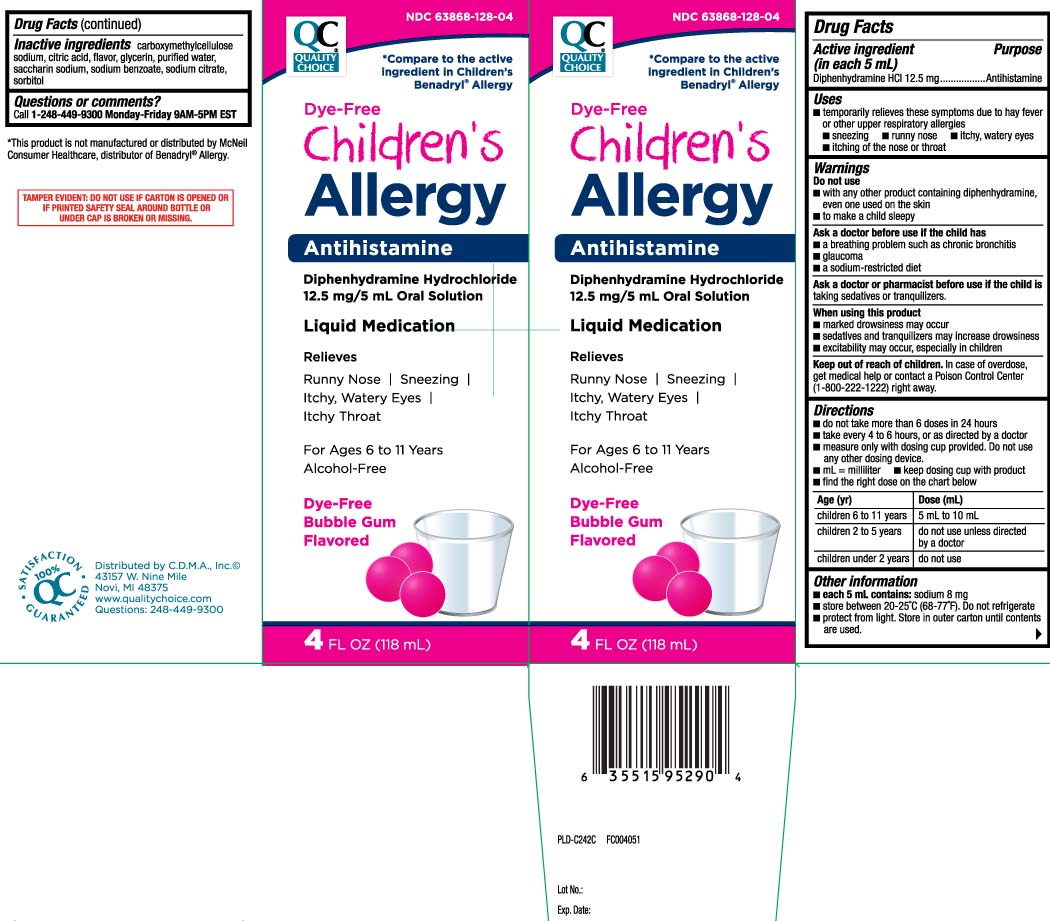 DRUG LABEL: Dye Free Allergy
NDC: 63868-128 | Form: LIQUID
Manufacturer: QUALITY CHOICE (Chain Drug Marketing Association)
Category: otc | Type: HUMAN OTC DRUG LABEL
Date: 20240422

ACTIVE INGREDIENTS: DIPHENHYDRAMINE HYDROCHLORIDE 12.5 mg/5 mL
INACTIVE INGREDIENTS: ANHYDROUS CITRIC ACID; GLYCERIN; WATER; SODIUM BENZOATE; TRISODIUM CITRATE DIHYDRATE; CARBOXYMETHYLCELLULOSE SODIUM; SACCHARIN SODIUM; SORBITOL

Drug Facts

Active ingredient (in each 5 mL)

Diphenhydramine HCl 12.5 mg

Purpose

Antihistamine

Uses

temporarily relieves these symptoms due to hay fever or other upper respiratory allergies:

- sneezing
- runny nose
- itchy, watery eyes
- itching of the nose or throat

Warnings

Do not use

- with any other product containing diphenhydramine, even one used on skin
- to make a child sleepy

Ask a doctor before use if the child has

- a breathing problem such as chronic bronchitis
- glaucoma
- a sodium-restricted diet

Ask a doctor or pharmacist before use if the child is

taking sedatives or tranquilizers

When using this product

- marked drowsiness may occur
- sedatives and tranquilizers may increase drowsiness
- excitability may occur, especially in children

Keep out of reach of children.

In case of overdose, get medical help or contact a Poison Control Center (1-800-222-1222) right away.

Directions

- do not take more than 6 doses in 24 hours
- take every 4 to 6 hours, or as directed by a doctor
- measure only with dosing cup provided. Do not use any other dosing device.
- mL = milliliter
- keep dosing cup with product
- find the right dose on the chart below

age (yr) | dose (mL)
children 6 to 11 years | 5 mL to 10 mL
children 2 to 5 years | do not use unless directed by a doctor
children under 2 years | do not use

Other information

- each 5 mL contains: sodium 8 mg
- store between 20-25°C (68-77°F). Do not refrigerate.
- Protect from light. Store in outer carton until contents are used.

Inactive ingredients

anhydrous citric acid, carboxymethycellulose sodium, flavor, glycerin, purified water, saccharin sodium, sodium benzoate, sodium citrate, sorbitol

Questions or comments?

Call 1-248-449-9300 Monday-Friday 9AM-5PM EST

Principal Display Panel

*Compare to the active ingredient in Children's Benadryl® Allergy

Dye-Free

Children's

Allergy

Antihistamine

Diphenhydramine Hydrochloride 12.5mg / 5 mL Oral Solution

Liquid Medication

Relieves

Runny Nose | Sneezing |

Itchy, Watery Eyes | Itchy Throat

For Ages 6 to 11 Years

Alcohol-Free

Dye-Free

Bubble Gum Flavored

FL OZ (mL)

*This product is not manufactured or distributed by McNeil Consumer Healthcare, distributors of Benadryl® Allergy.

TAMPER EVIDENT: DO NOT USE IF CARTON IS OPENED OR IF PRINTED SAFETY SEAL AROUND BOTTLE OR UNDER CAP IS BROKEN OR MISSING.

Distributed by C.D.M.A., Inc,©

43157 W.Nine Mile

Novi, MI 48376-0995

www.qualitychoice.com

Package Label

QUALITY CHOICE Dye-Free Children's Allergy